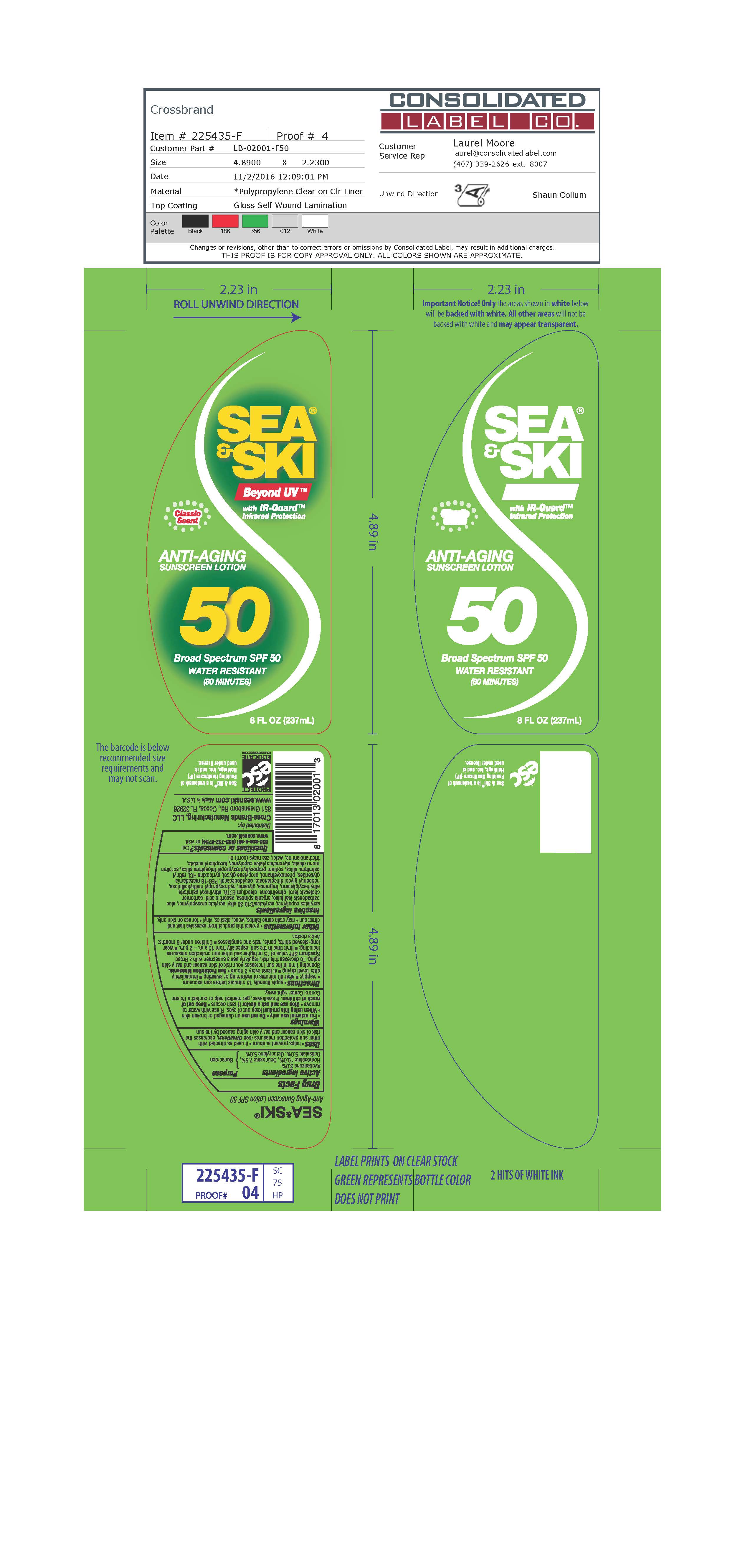 DRUG LABEL: General Protection
NDC: 71153-2001 | Form: LOTION
Manufacturer: Cross-Brands Manufacturing, LLC
Category: otc | Type: HUMAN OTC DRUG LABEL
Date: 20161222

ACTIVE INGREDIENTS: OCTISALATE 5 g/1 mL; OCTOCRYLENE 5 g/1 mL; OCTINOXATE 7.5 g/1 mL; AVOBENZONE 3 g/1 mL; HOMOSALATE 10 g/1 mL
INACTIVE INGREDIENTS: ALOE VERA LEAF

Sea & Ski GP Sunscreen Lotion SPF 50